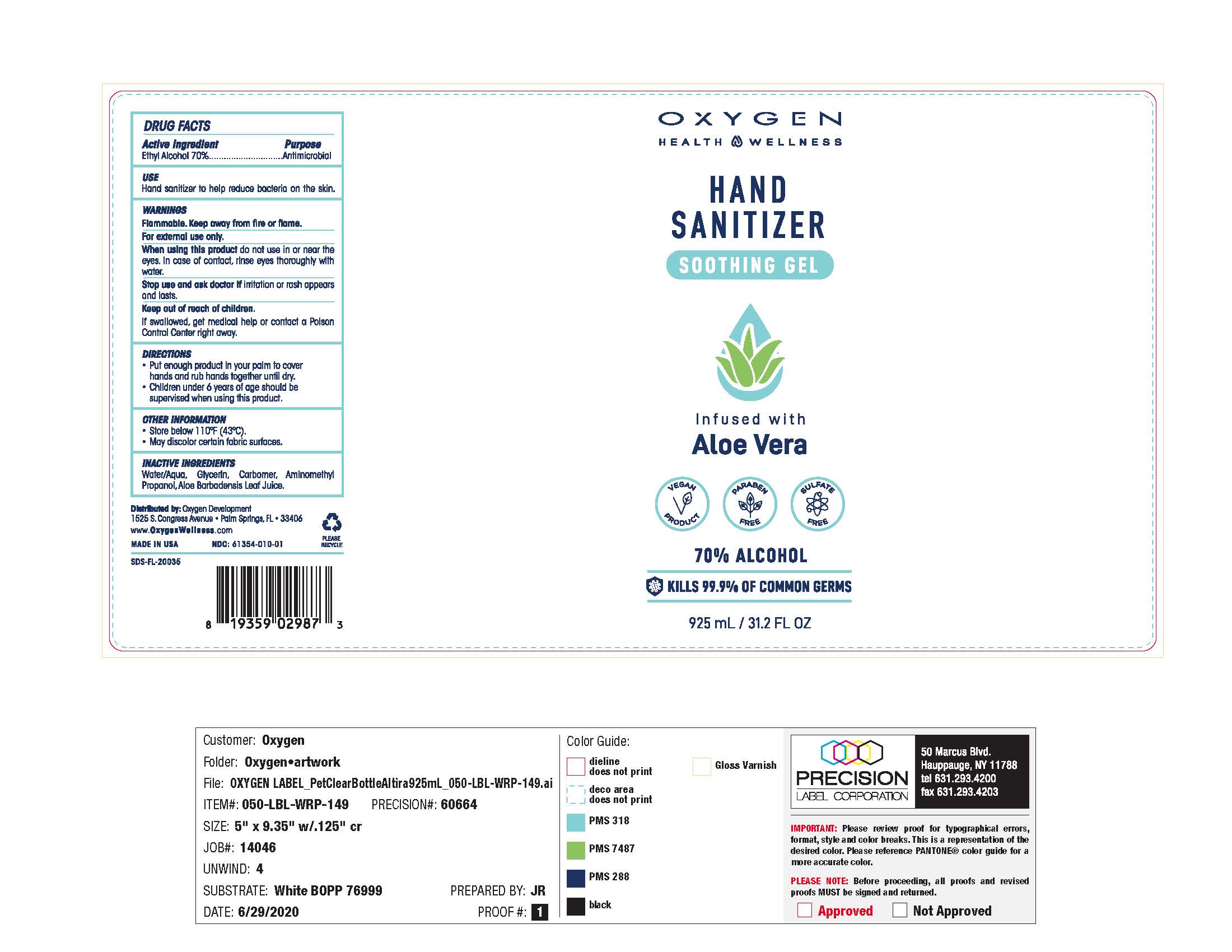 DRUG LABEL: Hand Sanitizer
NDC: 61354-044 | Form: GEL
Manufacturer: Oxygen Development LLC
Category: otc | Type: HUMAN OTC DRUG LABEL
Date: 20220111

ACTIVE INGREDIENTS: ALCOHOL 70.47 mL/100 mL
INACTIVE INGREDIENTS: GLYCERIN 1.49 mL/100 mL; CARBOMER HOMOPOLYMER, UNSPECIFIED TYPE 0.5 mL/100 mL; WATER 27.44 mL/100 mL

Oxygen Health Wellness Hand Sanitizer infused with Aloe Vera 70% Alcohol

Active Ingredient(s)

Ethyl Alcohol 70%

Purpose

Antimicrobial

Use

Hand Sanitizer to help reduce bacteria on the skin.

Warnings

Flammable. Keep away from heat or flame. For external use only.

When using

When using this product do not use in or near the eyes, rinse eyes thoroughly with water.
Stop use and ask a doctor if irritation or rash appears and lasts.

Keep out of reach of children. If swallowed, get medical help or contact a Poison Control Center right away.

Stop use

Stop use and ask a doctor if irritation or rash appears and lasts.

Keep out of reach of children

If swallowed, get medical help or contact a Poison Control Center right away.

Directions

- Put enough product in your palm to cover hands and rub hands together until dry.
- Children under 6 years of age should be supervised when using this product.

Other information

- Store below 110F (43C)
- May discolor certain fabric surfaces.

Inactive ingredients

Water / aqua, Glycerin, Carbomer, Aminomethyl Propanol, Aloe Barbadensis Leaf Juice.